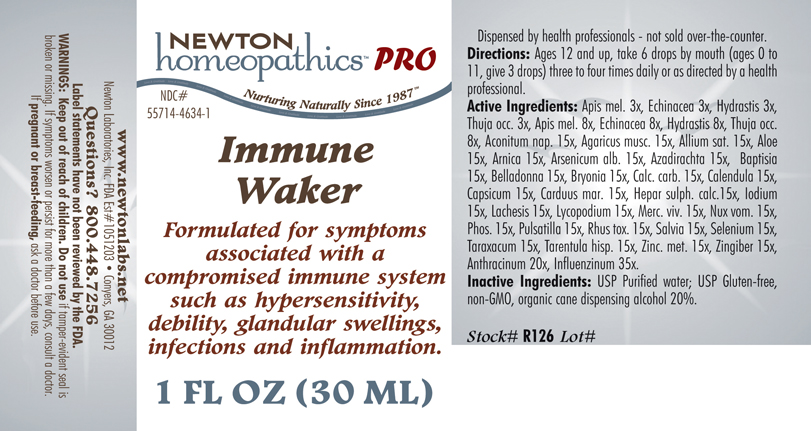 DRUG LABEL: Immune Waker 
NDC: 55714-4634 | Form: LIQUID
Manufacturer: Newton Laboratories, Inc.
Category: homeopathic | Type: HUMAN PRESCRIPTION DRUG LABEL
Date: 20141110

ACTIVE INGREDIENTS: Apis Mellifera 8 [hp_X]/1 mL; Echinacea, Unspecified 8 [hp_X]/1 mL; Goldenseal 8 [hp_X]/1 mL; Thuja Occidentalis Leafy Twig 8 [hp_X]/1 mL; Aconitum Napellus 15 [hp_X]/1 mL; Amanita Muscaria Fruiting Body 15 [hp_X]/1 mL; Garlic 15 [hp_X]/1 mL; Aloe 15 [hp_X]/1 mL; Arnica Montana 15 [hp_X]/1 mL; Arsenic Trioxide 15 [hp_X]/1 mL; Azadirachta Indica Bark 15 [hp_X]/1 mL; Baptisia Tinctoria Root 15 [hp_X]/1 mL; Atropa Belladonna 15 [hp_X]/1 mL; Bryonia Alba Root 15 [hp_X]/1 mL; Oyster Shell Calcium Carbonate, Crude 15 [hp_X]/1 mL; Calendula Officinalis Flowering Top 15 [hp_X]/1 mL; Capsicum 15 [hp_X]/1 mL; Milk Thistle 15 [hp_X]/1 mL; Calcium Sulfide 15 [hp_X]/1 mL; Iodine 15 [hp_X]/1 mL; Lachesis Muta Venom 15 [hp_X]/1 mL; Lycopodium Clavatum Spore 15 [hp_X]/1 mL; Mercury 15 [hp_X]/1 mL; Strychnos Nux-vomica Seed 15 [hp_X]/1 mL; Phosphorus 15 [hp_X]/1 mL; Pulsatilla Vulgaris 15 [hp_X]/1 mL; Toxicodendron Pubescens Leaf 15 [hp_X]/1 mL; Sage 15 [hp_X]/1 mL; Selenium 15 [hp_X]/1 mL; Taraxacum Officinale 15 [hp_X]/1 mL; Lycosa Tarantula 15 [hp_X]/1 mL; Zinc 15 [hp_X]/1 mL; Ginger 15 [hp_X]/1 mL; Bacillus Anthracis 20 [hp_X]/1 mL; Influenza A Virus 35 [hp_X]/1 mL; Influenza B Virus 35 [hp_X]/1 mL
INACTIVE INGREDIENTS: Alcohol; Water

Immune Waker

INDICATIONS & USAGE SECTION

Formulated for symptoms associated with a compromised immune system such as hypersensitivity, debility, glandular swellings, infections and inflammation.

DOSAGE & ADMINISTRATION SECTION

Directions: Ages 12 and up, take 6 drops by mouth (ages 0 to11, give 3 drops) three to four times daily or as directed by a health professional.

ACTIVE INGREDIENT SECTION

Apis mel. 3x, Echinacea 3x, Hydrastis 3x, Thuja occ. 3x, Apis mel. 8x, Echinacea 8x, Hydrastis 8x, Thuja occ. 8x, Aconitum nap. 15x, Agaricus musc. 15x, Allium sat. 15x, Aloe 15x, Arnica 15x, Arsenicum alb. 15x, Azadirachta 15x, Baptisia 15x, Belladonna 15x, Bryonia 15x, Calc. carb. 15x, Calendula 15x, Capsicum 15x, Carduus mar. 15x, Hepar sulph. calc. 15x, Iodium 15x, Lachesis 15x, Lycopodium 15x, Merc. viv. 15x, Nux vom. 15x, Phos. 15x, Pulsatilla 15x, Rhus tox. 15x,. Salvia 15x, Selenium 15x, Taraxacum 15x, Tarentula hisp. 15x, Zinc. met. 15x, Zingiber 15x, Anthracinum 20x, Influenzinum 35x.

PURPOSE SECTION

Formulated for symptoms associated with a compromised immune system such as hypersensitivity, debility, glandular swellings, infections and inflammation.

INACTIVE INGREDIENT SECTION

Inactive Ingredients: USP Purified Water; USP Gluten-free, non-GMO, organic cane dispensing alcohol 20%.

QUESTIONS SECTION

www.newtonlabs.net Newton Laboratories, Inc. FDA Est # 1051203 - Conyers, GA 30012 Questions? 1.800.448.7256

WARNINGS SECTION

Warning: Keep out of reach of children. Do not use if tamper-evident seal is broken or missing. If symptoms worsen or persist for more than a few days, consult a doctor. If pregnant or breast-feeding, ask a doctor before use.

PREGNANCY OR BREAST FEEDING SECTION

If pregnant or breast-feeding, ask a doctor before use.

KEEP OUT OF REACH OF CHILDREN SECTION

Keep out of reach of children.